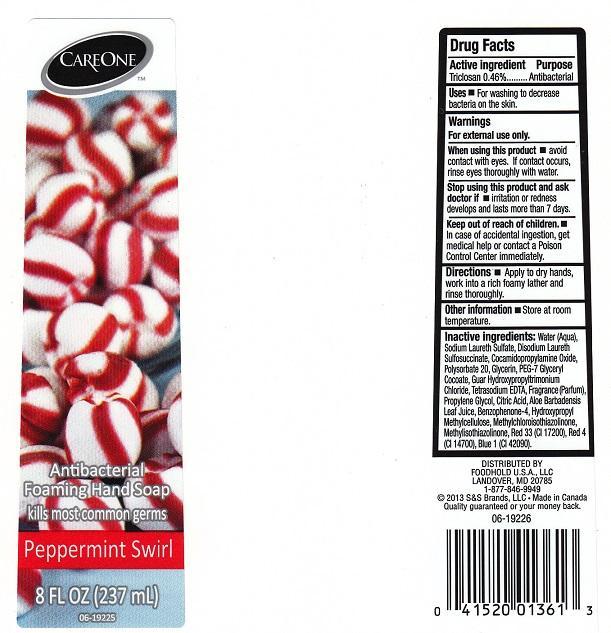 DRUG LABEL: CARE ONE
NDC: 41520-119 | Form: LIQUID
Manufacturer: AMERICAN SALES COMPANY
Category: otc | Type: HUMAN OTC DRUG LABEL
Date: 20131028

ACTIVE INGREDIENTS: TRICLOSAN 4.6 mg/1 mL
INACTIVE INGREDIENTS: WATER; SODIUM LAURETH SULFATE; DISODIUM LAURETH SULFOSUCCINATE; COCAMIDOPROPYLAMINE OXIDE; POLYSORBATE 20; GLYCERIN; PEG-7 GLYCERYL COCOATE; GUAR HYDROXYPROPYLTRIMONIUM CHLORIDE (1.7 SUBSTITUENTS PER SACCHARIDE); EDETATE SODIUM; PROPYLENE GLYCOL; CITRIC ACID MONOHYDRATE; ALOE VERA LEAF; SULISOBENZONE; HYPROMELLOSES; METHYLCHLOROISOTHIAZOLINONE; METHYLISOTHIAZOLINONE; D&C RED NO. 33; FD&C RED NO. 4; FD&C BLUE NO. 1

DRUG FACTS

ACTIVE INGREDIENT

TRICLOSAN 0.46%

PURPOSE

ANTIBACTERIAL

USES

FOR WASHING TO DECREASE BACTERIA ON THE SKIN

WARNINGS

FOR EXTERNAL USE ONLY

WHEN USING THIS PRODUCT

AVOID CONTACT WITH EYES. IF CONTACT OCCURS, RINSE EYES THOROUGHLY WITH WATER

STOP USING THIS PRODUCT AND ASK DOCTOR IF

IRRITATION OR REDNESS DEVELOPS AND LASTS MORE THAN 7 DAYS

KEEP OUT OF REACH OF CHILDREN

IN CASE OF ACCIDENTAL INGESTION, GET MEDICAL HELP OR CONTACT A POISON CONTROL CENTER IMMEDIATELY

DIRECTIONS

APPLY TO DRY HANDS, WORK INTO A RICH FOAMY LATHER AND RINSE THOROUGHLY

OTHER INFORMATION

STORE AT ROOM TEMPERATURE

INACTIVE INGREDIENTS

WATER (AQUA), SODIUM LAURETH SULFATE, DISODIUM LAURETH SULFOSUCCINATE, COCAMIDOPROPYLAMINE OXIDE, POLYSORBATE 20, GLYCERIN, PEG-7 GLYCERYL COCOATE, GUAR HYDROXYPROPYLTRIMONIUM CHLORIDE, TETRASODIUM EDTA, FRAGRANCE (PARFUM), PROPYLENE GLYCOL, CITRIC ACID, ALOE BARBADENSIS LEAF JUICE, BENZOPHENONE-4, HYDROXYPROPYL METHYLCELLULOSE, METHYLCHLOROISOTHIAZOLINONE, METHYLISOTHIAZOLINONE, RED 33 (CI 17200), RED 4 (CI 14700), BLUE 1 (CI 42090)